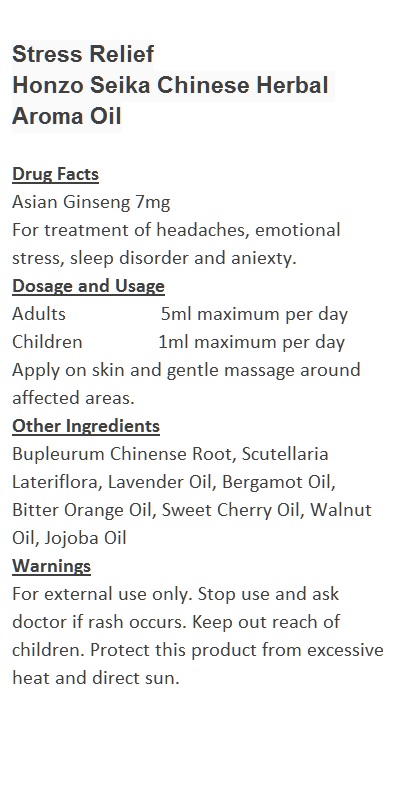 DRUG LABEL: Stress Relief	
NDC: 70470-9901 | Form: OIL
Manufacturer: Phytopia Co., Ltd.
Category: otc | Type: HUMAN OTC DRUG LABEL
Date: 20170101

ACTIVE INGREDIENTS: ASIAN GINSENG 7 mg/100 mL
INACTIVE INGREDIENTS: SCUTELLARIA LATERIFLORA; BITTER ORANGE OIL; SWEET CHERRY SEED OIL; WALNUT OIL; JOJOBA OIL; BERGAMOT OIL; LAVENDER OIL; BUPLEURUM CHINENSE ROOT

Drug Facts

Asian Ginseng 7mg

Use

For treatment of headaches, emotional stress, sleep disorder and aniexty.

Dosage Suggestion

Adults 5ml maximum per day

Children 1ml maximum per day

INACTIVE INGREDIENT

Other Ingredients

Bupleurum Chinense Root, Scutellaria Lateriflora, Lavender Oil, Bergamot Oil, Bitter Orange Oil, Sweet Cherry Oil, Walnut Oil, Jojoba Oil

Directions

Apply on skin and gentle massage around affected area.

Warnings

For external use only. Stop use and ask doctor if rash occurs. Keep out reach of children.

Other Information

Protect this product from excessive heat

and direct sun.

Warnings

For external use only. Stop use and ask doctor if rash occurs. Keep out reach of children.